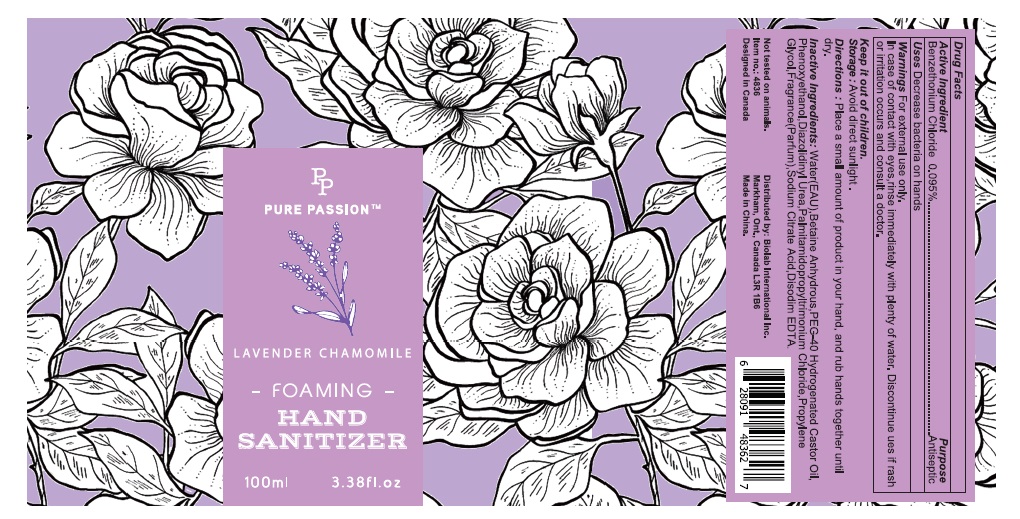 DRUG LABEL: Hand Sanitizer
NDC: 72264-002 | Form: GEL
Manufacturer: Biolab International Incorporated
Category: otc | Type: HUMAN OTC DRUG LABEL
Date: 20180419

ACTIVE INGREDIENTS: BENZETHONIUM CHLORIDE 0.095 g/100 mL
INACTIVE INGREDIENTS: DIAZOLIDINYL UREA; BETAINE; PROPYLENE GLYCOL; WATER; PALMITAMIDOPROPYLTRIMONIUM CHLORIDE; DISODIUM HYDROGEN CITRATE; EDETATE DISODIUM ANHYDROUS; PHENOXYETHANOL; POLYOXYL 40 HYDROGENATED CASTOR OIL

Active Ingredient
Benzethonium Chloride 0.095%

Purpose

Antiseptic

Keep it out of children.

DOSAGE AND ADMINISTRATION

Directions: Place a small amount of product in your hand, and rub hands together until dry.

INACTIVE INGREDIENT

Inactive Ingredients: Water(EAU), Betaine Anhydrous,PEG-40 Hydrogenated Castor Oil, Phenoxyethanol,Diazolidinyl Urea, Palmitamidopropyltrimonium Chloride, Propylene Glycol, Fragrance(Parfum), Sodium Citric Acid, Disodium EDTA.

Storage: Avoid direct sunlight.

Uses

Decrease bacteria on hands.

WARNINGS

WarningsFor external use only.

In case of contact with eyes, rinse immediately with plenty of water. Discontinue use if rash or irritation occurs and consult a doctor.